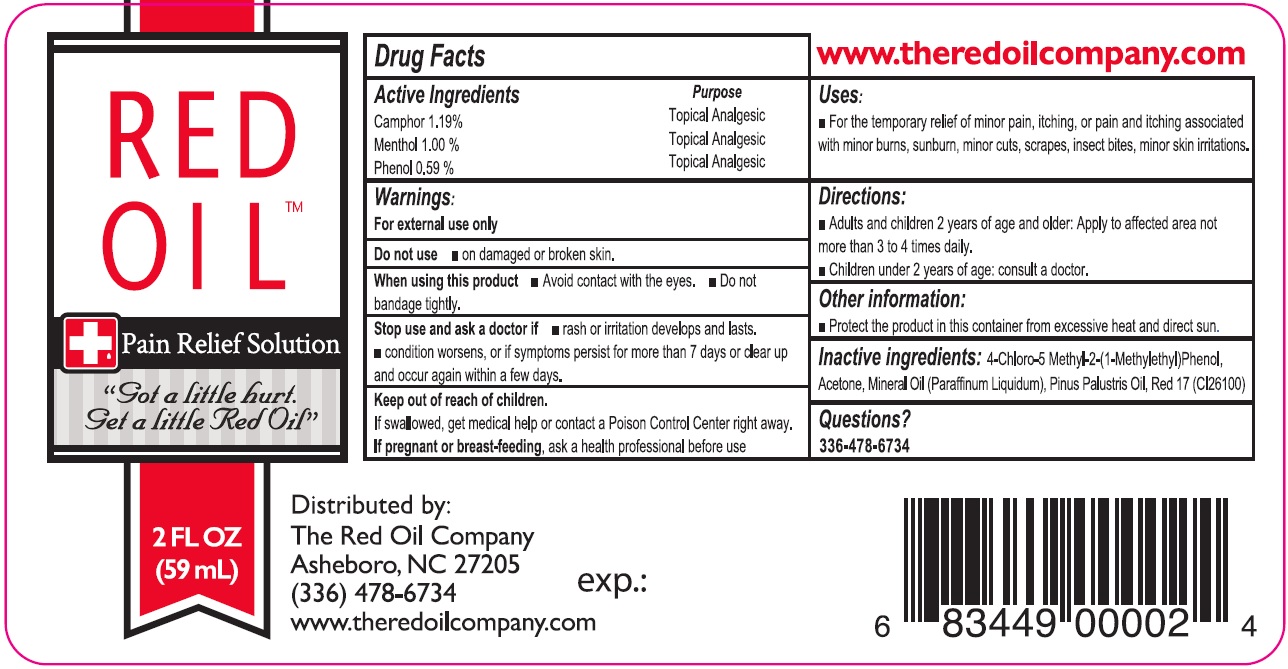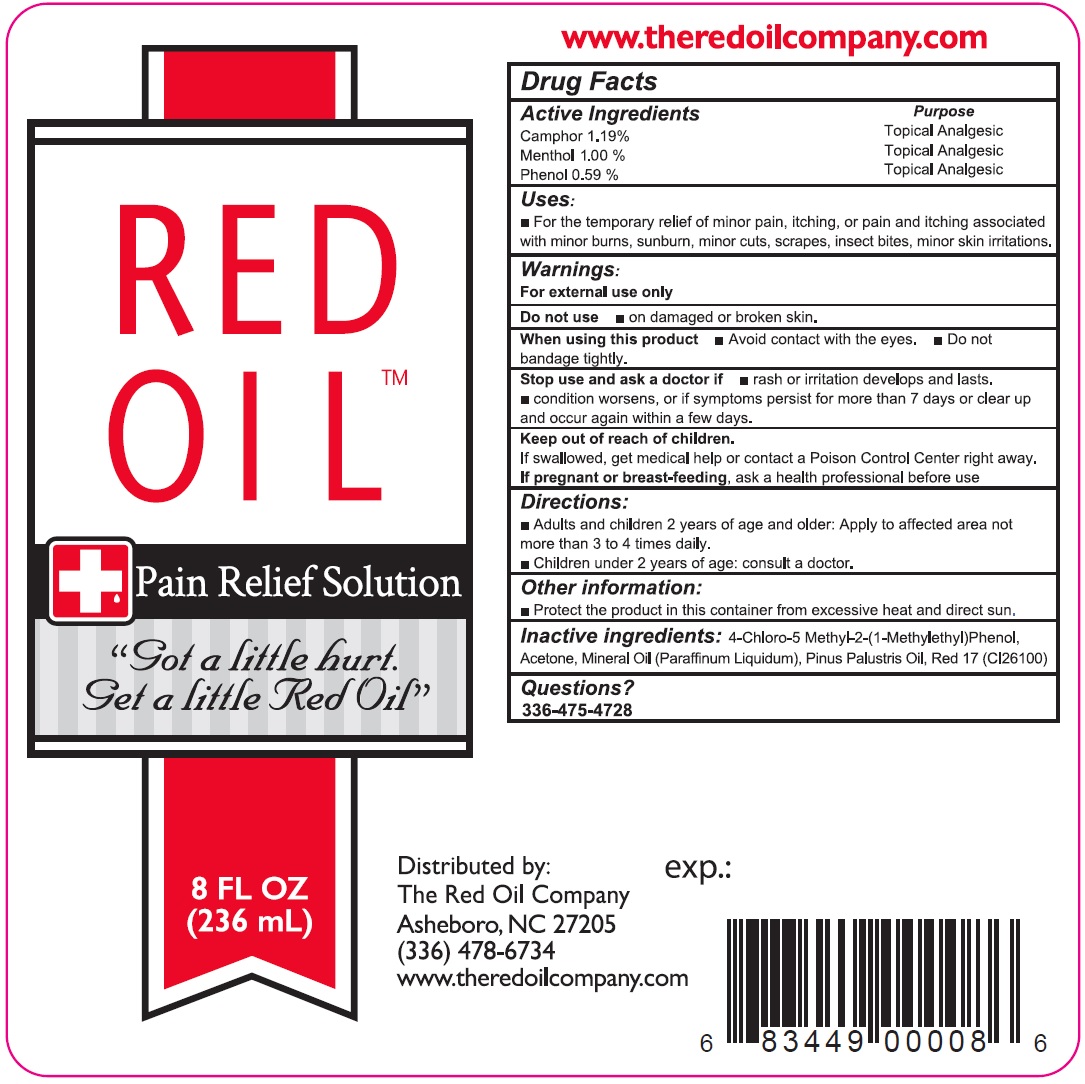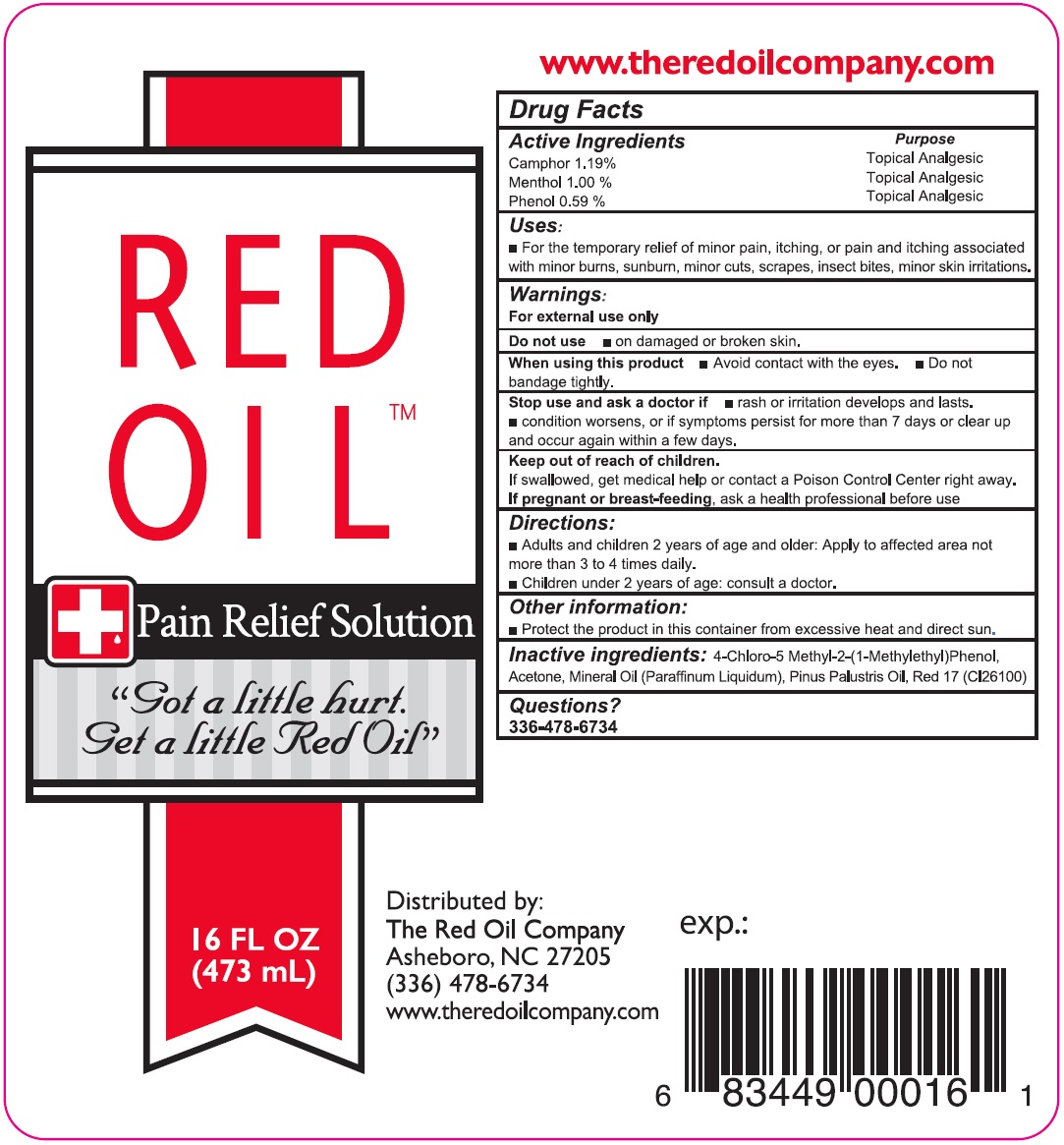 DRUG LABEL: Red Oil Pain Relief
NDC: 70537-986 | Form: SOLUTION
Manufacturer: The Red Oil Company Inc
Category: otc | Type: HUMAN OTC DRUG LABEL
Date: 20260129

ACTIVE INGREDIENTS: CAMPHOR (SYNTHETIC) 11.9 mg/1 mL; MENTHOL 100 mg/1 mL; PHENOL 5.9 mg/1 mL
INACTIVE INGREDIENTS: CHLOROTHYMOL; ACETONE; MINERAL OIL; D&C RED NO. 17

Red Oil Pain Relief Solution

Active Ingredients

Camphor 1.19%
Menthol 10.00%
Phenol 0.59%

Purpose

Topical Analgesic

Uses:

For the temporary relief of minor pain, itching, or pain and itching associated with minor burns, sunburn, minor cuts, scrapes, insect bites, minor skin irritations.

Warnings:

For external use only

Do not use

- on damaged or broken skin.

When using this product

- Avoid contact with the eyes.
- Do not bandage tightly.

Stop use and ask a doctor if

- rash or irritation develops and lasts.
- condition worsens, or if symptoms persist for more than 7 days or clear up and occur again with in a few days.

Keep out of reach of children.

If swallowed, get medical help or contact a Poison Control Center right away.

If pregnant or breast-feeding,

ask a health professional before use

Directions:

- Adults and children 2 years of age and older: Apply to affected area not more than 3 to 4 times daily.
- Children under 2 years of age: consult a doctor.

Other information:

- Protect the product in this container from excessive heat and direct sun.

Inactive ingredients:

4-Chloro-5 Methyl-2-(1-Methylethyl) Phenol, Acetone, Mineral Oil (Paraffinum Liquidum), Pinus Palustris Oil, Red 17 (CI 26100)

Questions?

336-478-6734